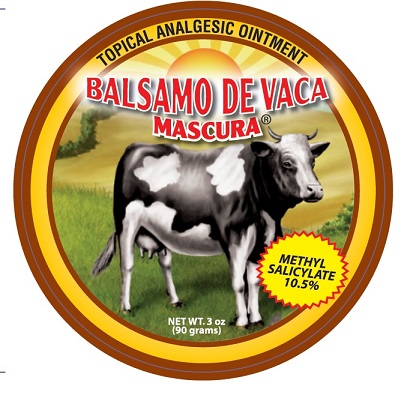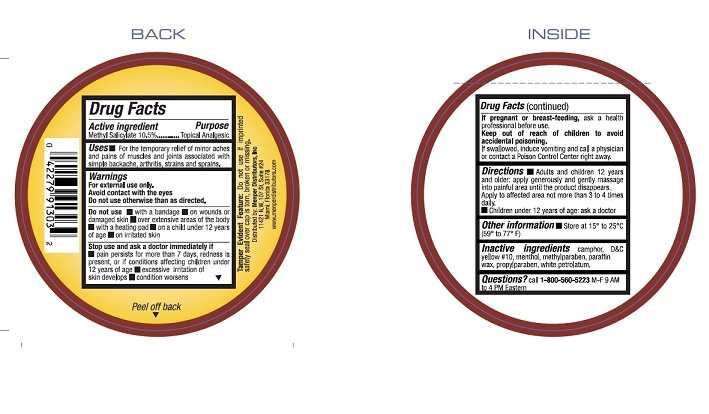 DRUG LABEL: Balsamo de Ubre
NDC: 53145-401 | Form: OINTMENT
Manufacturer: Menper Distributors Inc.
Category: otc | Type: HUMAN OTC DRUG LABEL
Date: 20220218

ACTIVE INGREDIENTS: METHYL SALICYLATE 10.5 g/90 g
INACTIVE INGREDIENTS: CAMPHOR (NATURAL); D&C YELLOW NO. 10; MENTHOL; METHYLPARABEN; PARAFFIN; PROPYLPARABEN; PETROLATUM

Active Ingredient

Methyl Salicylate 10.5 % ............................................Topical Analgesic

Uses

Topical Analgesic

Uses

For the temporary relief of minor aches and pains of muscles and joints associated with simple backache, arthritis, strains and sprains

Warnings

For external use only.

Avoid contact with the eyes.

Do not use otherwise than as directed

Do not use with a heating pad

- with a bandage
- on wounds or dasmage skin
- over extensive areas of the body
- with a heating pad
- on a child under 12 years of age
- on irritated skin

Stop use and ask a doctor immediately if

- pain persists for more than 7 days, redness is present, or in conditions affecting children under 12 years of age
- excessive irritation of skin develops
- condition worsens

If pregnant or breast-feeding,

ask a health professional before use.

Keep out of reach of children to avoid accidental poisoning.

If swallowed, induce vomiting and call a physician or contact a Poison Control Center right away.

Directions

- Adults and Children 12 years and older: apply generously and gently massage into painful area until the product disappears. Apply into affected area not more than 3 to 4 times daily
- Children under 12 years of age: ask a doctor

Other Information

Store at 15° C to 25° C (59° F to 77° F)

Inactive ingrediets

camphor, D&C yellow #10, menthol, methylparaben, paraffin wax, propylparaben, white petrolatum.

Questions?

call 1-800-560-5223 M-F 9 AM to 4 PM Eastern